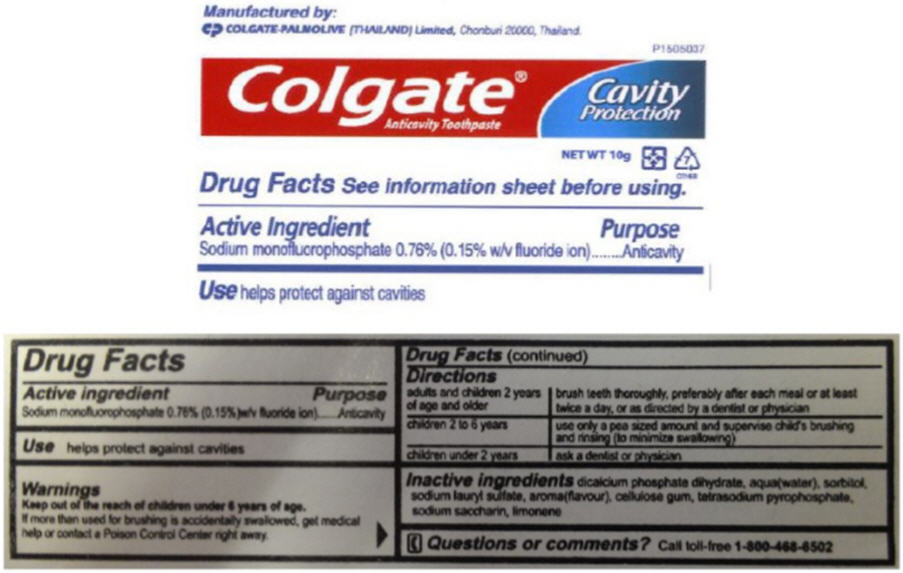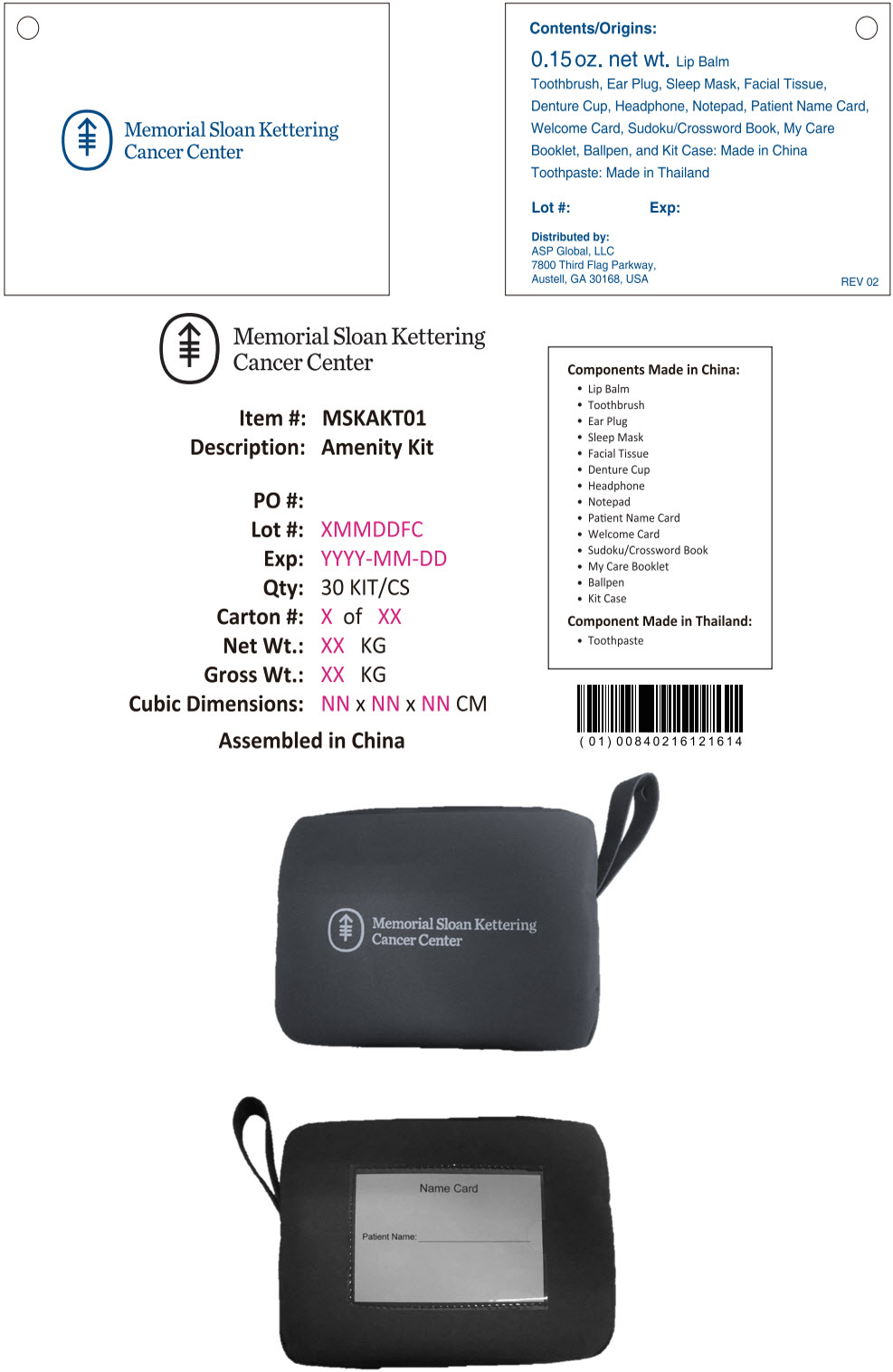 DRUG LABEL: Memorial Sloan Kettering Cancer Center Amenity Kit
NDC: 59448-300 | Form: KIT | Route: DENTAL
Manufacturer: ASP Global, LLc
Category: otc | Type: HUMAN OTC DRUG LABEL
Date: 20241217

ACTIVE INGREDIENTS: Sodium Monofluorophosphate 7.6 mg/1 g
INACTIVE INGREDIENTS: Dibasic Calcium Phosphate Dihydrate; Water; Sorbitol; Sodium Lauryl Sulfate; Carboxymethylcellulose Sodium, Unspecified; Sodium Pyrophosphate; Saccharin Sodium

Memorial Sloan Kettering Cancer Center Amenity Kit

Drug Facts

Active ingredient

Sodium monofluorophosphate 0.76% (0.15%)w/v fluoride ion)

Purpose

Anticavity

Use

helps protect against cavities

Warnings

KEEP OUT OF REACH OF CHILDREN

Keep out of the reach of children under 6 years of age.

If more than used for brushing is accidentally swallowed, get medical help or contact a Poison Control Center right away.

Directions

adults and children 2 years of age and older | brush teeth thoroughly, preferably after each meal or at least twice a day, or as directed by a dentist or physician
children 2 to 6 years | use only a pea sized amount and supervise child's brushing and rinsing (to minimize swallowing)
children under 2 years | ask a dentist or physician

Inactive ingredients

dicalcium phosphate dihydrate, aqua(water), sorbitol, sodium lauryl sulfate, aroma(flavour), cellulose gum, tetrasodium pyrophosphate, sodium saccharin, limonene

Questions or comments?

Call toll-free 1-800-468-6502

Manufactured by:
COLGATE-PALMOLIVE (THAILAND) Limited, Chonburi 20000, Thailand.

PRINCIPAL DISPLAY PANEL - 10 g Tube Label

P1505037

Colgate®
Anticavity Toothpaste

Cavity
Protection

NET WT 10g

7
OTHER

PRINCIPAL DISPLAY PANEL - Kit Label

Memorial Sloan Kettering
Cancer Center

Contents/Origins:

0.15 oz. net wt. Lip Balm
Toothbrush, Ear Plug, Sleep Mask, Facial Tissue,
Denture Cup, Headphone, Notepad, Patient Name Card,
Welcome Card, Sudoku/Crossword Book, My Care
Booklet, Ballpen, and Kit Case: Made in China
Toothpaste: Made in Thailand

Lot #:
Exp:

Distributed by:
ASP Global, LLC
7800 Third Flag Parkway,
Austell, GA 30168, USA
REV 02

Memorial Sloan Kettering
Cancer Center

Item #: MSKAKT01
Description: Amenity Kit

PO #:
Lot #: XMMDDFC
Exp: YYYY-MM-DD
Qty: 30 KIT/CS
Carton #: X of XX
Net Wt.: XX KG
Gross Wt.: XX KG
Cubic Dimensions: NN x NN x NN CM

Assembled in China

Components Made in China:

- Lip Balm
- Toothbrush
- Ear Plug
- Sleep Mask
- Facial Tissue
- Denture Cup
- Headphone
- Notepad
- Patient Name Card
- Welcome Card
- Sudoku/Crossword Book
- My Care Booklet
- Ballpen
- Kit Case

Component Made in Thailand:

- Toothpaste

Memorial Sloan Kettering
Cancer Center

Name Card

Patient Name: